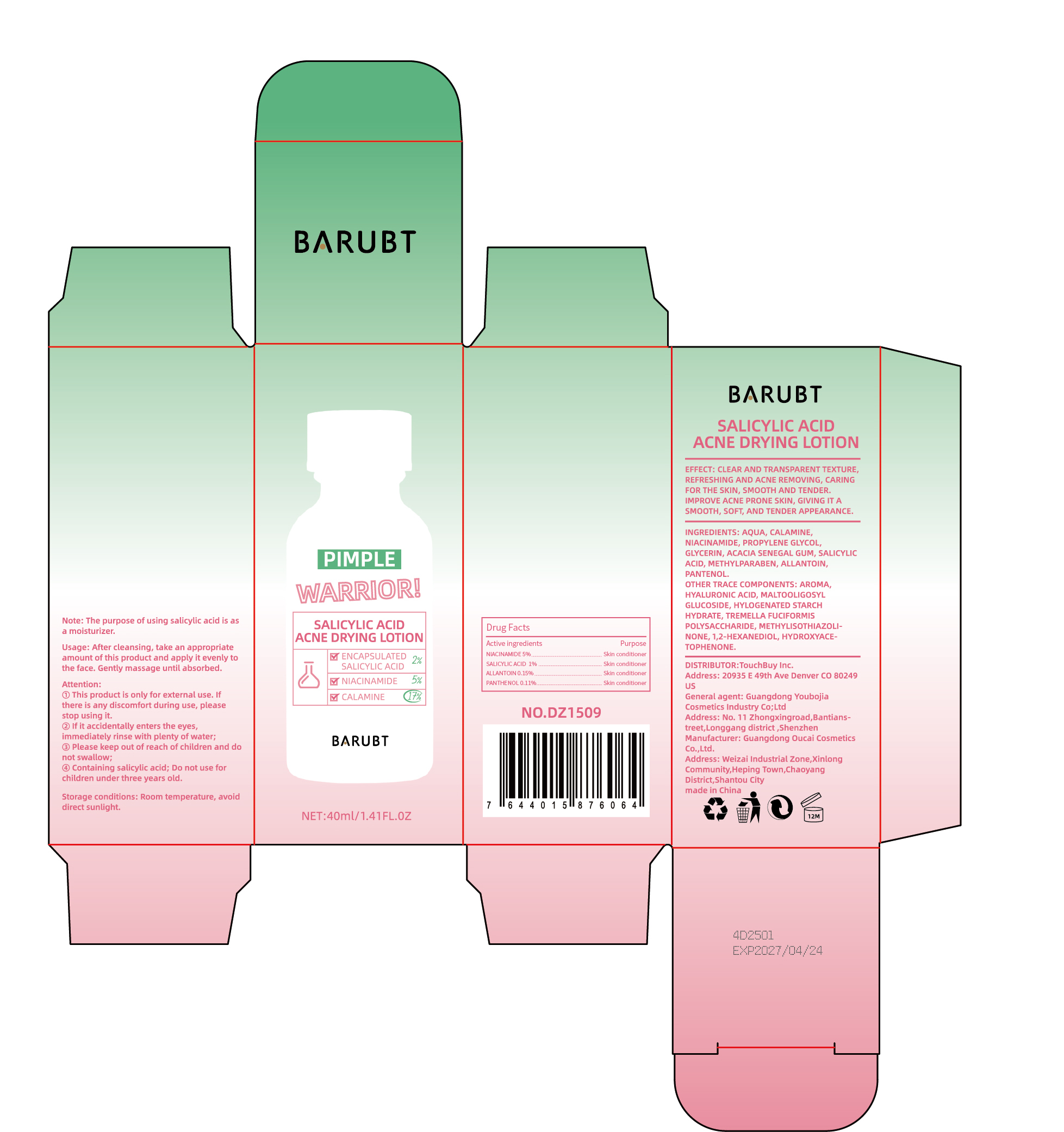 DRUG LABEL: BARUBY SALICYLIC ACID ACNE DRYING
NDC: 84712-010 | Form: LOTION
Manufacturer: Guangdong Youbaijia Cosmetic Industry Co., Ltd
Category: otc | Type: HUMAN OTC DRUG LABEL
Date: 20240913

ACTIVE INGREDIENTS: ALLANTOIN 0.06 g/40 mL; PANTHENOL 0.044 g/40 mL; NIACINAMIDE 2 g/40 mL; SALICYLIC ACID 0.4 g/40 mL
INACTIVE INGREDIENTS: GLYCERIN 0.4 g/40 mL; METHYLPARABEN 0.08 g/40 mL

ACTIVE INGREDIENT

NIACINAMIDE 5%
SALICYLIC ACID 1%
ALLANTOIN 0.15%
PANTHENOL 0.11%

DO NOT USE

on damaged or broken skin

INACTIVE INGREDIENT

AQUA
CALAMINE
PROPYLENE GLYCOL
GLYCERIN
ACACIA SENEGAL GUM
METHYLPARABEN
AROMA
HYALURONIC ACID
MALTOOLIGOSYL GLUCOSIDE
HYLOGENATED STARCH HYDRATE
TREMELLA FUCIFORMIS POLYSACCHARIDE
METHYLISOTHIAZOLINONE
1,2-HEXANEDIOL
HYDROXYACETOPHENONE

Keep away from children. Do not swallow.

PURPOSE

ACNE REMOVING

STOP USE

lf there is any discomfort during use, please stop using it.

WHEN USING

lf it accidentally enters the eyes,immediately rinse with plenty of water;

QUESTIONS

Contact name: Jessie Peng
Company phone number: +1 818 579 7288
Company e-mail: jessie@registeragentllc.com

STORAGE AND HANDLING

Room temperature, avoid direct sunlight.

WARNINGS

This product is only for external use.

Containing salicylic acid; Do not use forchildren under three years old.

INDICATIONS AND USAGE

CLEAR AND TRANSPARENT TEXTURE REFRESHING AND ACNE REMOVING, CARING FOR THE SKIN, SMOOTH AND TENDER.IMPROVE ACNE PRONE SKIN, GIVING IT A SMOOTH, SOFT AND TENDER APPEARANCE.

DOSAGE AND ADMINISTRATION

Usage: After cleansing, take an appropriate amount of this product and apply it evenly to the face. Gently massage until absorbed.